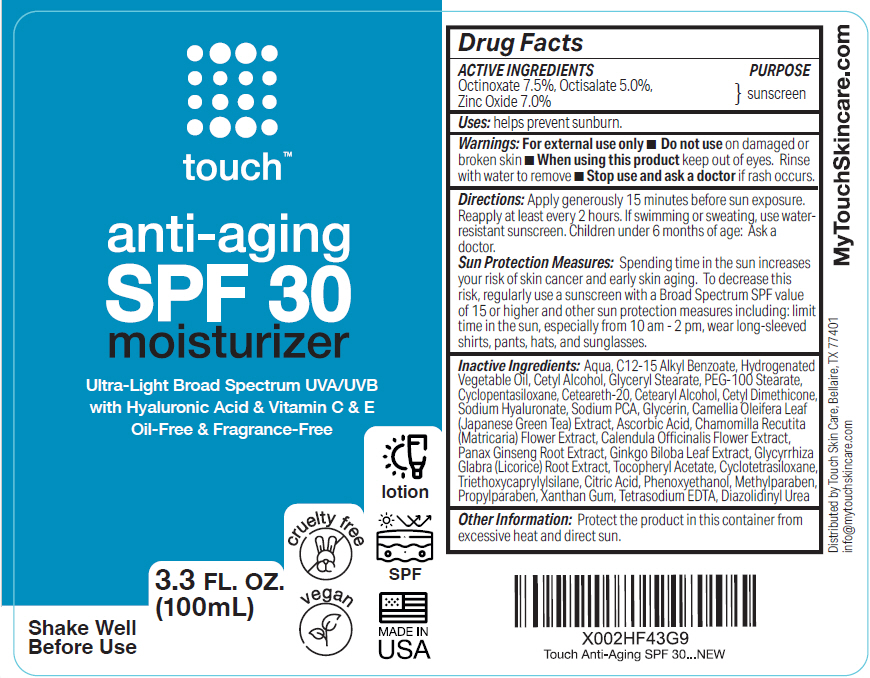 DRUG LABEL: Touch Anti-Aging SPF 30 Moisturizer
NDC: 73246-002 | Form: CREAM
Manufacturer: Diractions Capital LLC
Category: otc | Type: HUMAN OTC DRUG LABEL
Date: 20250710

ACTIVE INGREDIENTS: Zinc Oxide 70 mg/1 mL; Octinoxate 75 mg/1 mL; Octisalate 50 mg/1 mL
INACTIVE INGREDIENTS: Water; ALKYL (C12-15) BENZOATE; CETYL ALCOHOL; GLYCERYL MONOSTEARATE; CETOSTEARYL ALCOHOL; CETYL DIMETHICONE 45; ASCORBIC ACID; .ALPHA.-TOCOPHEROL ACETATE; CALENDULA OFFICINALIS FLOWER; MATRICARIA CHAMOMILLA FLOWERING TOP; GINKGO BILOBA WHOLE; PEG-100 STEARATE; CYCLOMETHICONE 5; POLYOXYL 20 CETOSTEARYL ETHER; PANAX GINSENG ROOT OIL; CAMELLIA OLEIFERA LEAF; GLYCYRRHIZA GLABRA; SODIUM PYRROLIDONE CARBOXYLATE; GLYCERIN; HYALURONATE SODIUM; CYCLOMETHICONE 4; TRIETHOXYCAPRYLYLSILANE; CITRIC ACID MONOHYDRATE; PHENOXYETHANOL; METHYLPARABEN; PROPYLPARABEN; XANTHAN GUM; EDETATE SODIUM; DIAZOLIDINYL UREA

Touch™ Anti-Aging SPF 30 Moisturizer

Drug Facts

ACTIVE INGREDIENTS

Octinoxate 7.5%, Octisalate 5.0%, Zinc Oxide 7.0%

PURPOSE

sunscreen

Uses

helps prevent sunburn.

Warnings

For external use only

- Do not use on damaged or broken skin

- When using this product keep out of eyes. Rinse with water to remove

- Stop use and ask a doctor if rash occurs.

Directions

Apply generously 15 minutes before sun exposure. Reapply at least every 2 hours. If swimming or sweating, use water-resistant sunscreen. Children under 6 months of age: Ask a doctor.

Sun Protection Measures

Spending time in the sun increases your risk of skin cancer and early skin aging. To decrease this risk, regularly use a sunscreen with a Broad Spectrum SPF value of 15 or higher and other sun protection measures including: limit time in the sun, especially from 10 am - 2 pm, wear long-sleeved shirts, pants, hats, and sunglasses.

Keep out of reach of children.

Inactive Ingredients

Aqua, C12-15 Alkyl Benzoate, Hydrogenated Vegetable Oil, Cetyl Alcohol, Glyceryl Stearate, PEG-100 Stearate, Cyclopentasiloxane, Ceteareth-20, Cetearyl Alcohol, Cetyl Dimethicone, Sodium Hyaluronate, Sodium PCA, Glycerin, Camellia Oleifera Leaf (Japanese Green Tea) Extract, Ascorbic Acid, Chamomilla Recutita (Matricaria) Flower Extract, Calendula Oﬃcinalis Flower Extract, Panax Ginseng Root Extract, Ginkgo Biloba Leaf Extract, Glycyrrhiza Glabra (Licorice) Root Extract, Tocopheryl Acetate, Cyclotetrasiloxane, Triethoxycaprylylsilane, Citric Acid, Phenoxyethanol, Methylparaben, Propylparaben, Xanthan Gum, Tetrasodium EDTA, Diazolidinyl Urea

Other Information

Protect the product in this container from excessive heat and direct sun.

Distributed by Touch Skin Care, Bellaire, TX 77401

PRINCIPAL DISPLAY PANEL - 100 mL Bottle Label

touch™

anti-aging
SPF 30
moisturizer

Ultra-Light Broad Spectrum UVA/UVB
with Hyaluronic Acid & Vitamin C & E
Oil-Free & Fragrance-Free

cruelty free
vegan

lotion
SPF
MADE IN
USA

Shake Well
Before Use

3.3 FL. OZ.
(100mL)